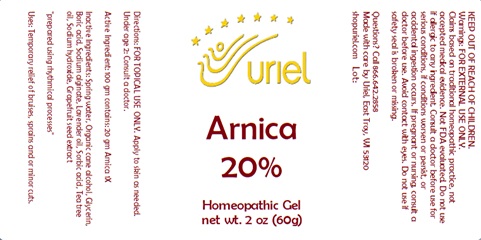 DRUG LABEL: Arnica 20%
NDC: 48951-1374 | Form: GEL
Manufacturer: Uriel Pharmacy Inc.
Category: homeopathic | Type: HUMAN OTC DRUG LABEL
Date: 20240328

ACTIVE INGREDIENTS: ARNICA MONTANA FLOWER 1 [hp_X]/1 g
INACTIVE INGREDIENTS: SODIUM ALGINATE; CITRUS PARADISI SEED; WATER; ALCOHOL; GLYCERIN; LAVENDER OIL; TEA TREE OIL; SORBIC ACID; SODIUM HYDROXIDE; BORIC ACID

Arnica 20%

INDICATIONS AND USAGE

Directions: FOR TOPICAL USE ONLY.

DOSAGE AND ADMINISTRATION

Apply to skin as needed. Under age 2: Consult a doctor.

Active Ingredient: 100 gm contains: 20 gm Arnica 1X

INACTIVE INGREDIENT

Inactive Ingredients: Spring water, Organic cane alcohol, Glycerin, Boric acid, Sodium alginate, Lavender oil, Sorbic acid, Tea tree oil, Sodium hydroxide, Grapefruit seed extract

PURPOSE

Uses: Temporary relief of bruises, sprains and or minor cuts.

prepared using rhythmical processes

KEEP OUT OF REACH OF CHILDREN.

Warnings: FOR EXTERNAL USE ONLY
Claims based on traditional homeopathic practice, not accepted medical evidence. Not FDA evaluated. Do not use if allergic to any ingredient. Consult a doctor before use for serious conditions, if conditions worsen or persist or accidental ingestion occurs. If pregnant or nursing consult a doctor before use. Avoid contact with eyes. Do not use if safety seal is broken or missing.

Questions? Call 866.642.2858
Made with care by Uriel, East Troy, WI 53120
shopuriel.com Lot: